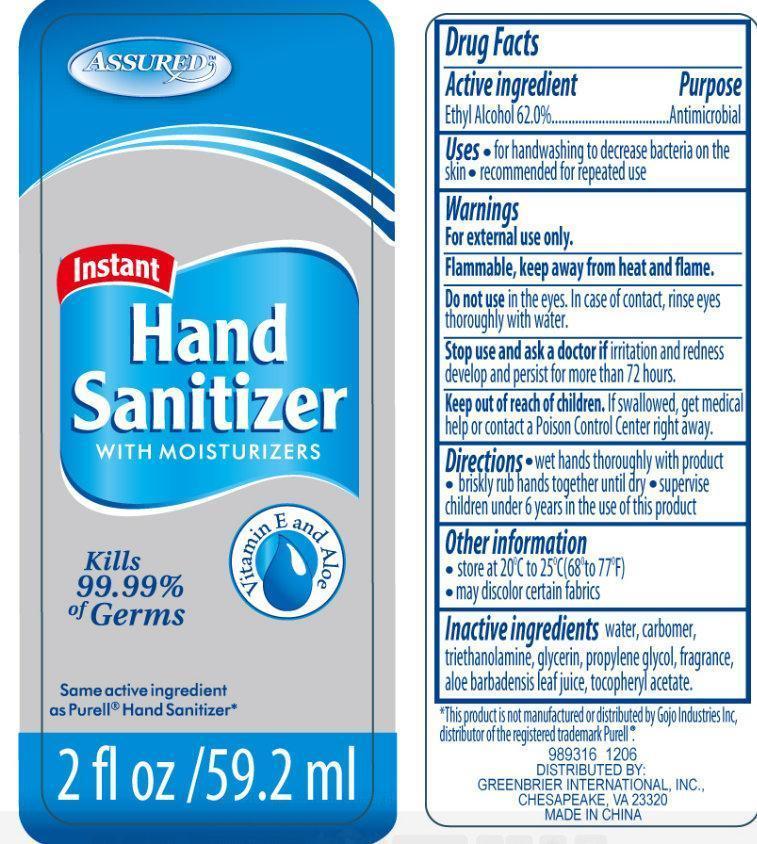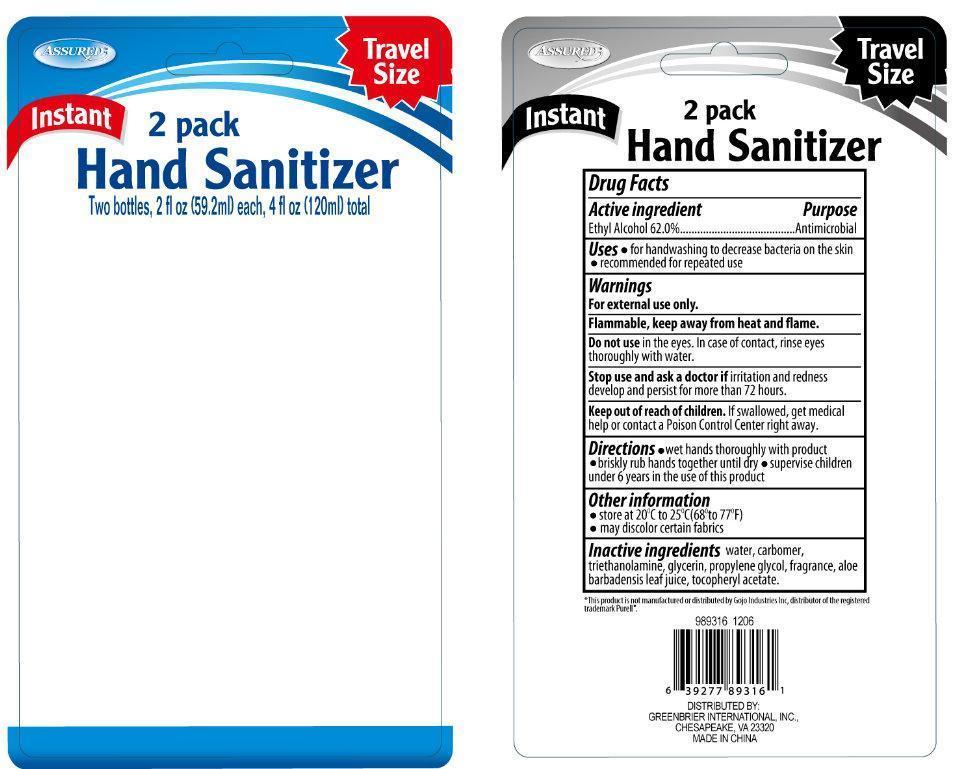 DRUG LABEL: Assured Instant Hand Sanitizer With Moisturizers Vitamin E and Aloe
NDC: 33992-1071 | Form: GEL
Manufacturer: Greenbrier International, Inc.
Category: otc | Type: HUMAN OTC DRUG LABEL
Date: 20190417

ACTIVE INGREDIENTS: ALCOHOL 62 mL/100 mL
INACTIVE INGREDIENTS: WATER; TROLAMINE; GLYCERIN; PROPYLENE GLYCOL; .ALPHA.-TOCOPHEROL ACETATE; ALOE VERA LEAF

Assured Instant Hand Sanitizer With Moisturizers Vitamin E and Aloe

WARNINGS AND PRECAUTIONS

Assured Instant Hand Sanitizer with Moisturizers Vitamin E and Aloe

Active Ingredient

Ethyl Alcohol 62.0%

Purpose

Antimicrobial

Uses

- for handwashing to decrease bacteria on the skin
- recommended for repeated use

Warnings

For external use only.

SAFE HANDLING WARNING

Flammable, keep away from heat and flame.

Do not use

in the eyes. In case of contact, rinse eyes thorougly with water.

Stop use and ask a doctor if

irritation and redness develop and persist for more than 72 hours.

Keep out of reach of children.

If swallowed, get medical help or contact a Poison Control Center right away.

Directions

- wet hands thoroughly with product
- briskly rub hands together until dry
- supervise children under 6 years in the use of this product

Other Information

- store at 20 degrees C (68 to 77 degrees F).
- may discolor certain fabrics.

Inactive Ingredients

water, carbomer, triethanolamine, glycerin, propylene glycol, fragrance, aloe barbadensis leaf juice, tocopheryl acetate.

DESCRIPTION

This product is not manufactured by Gojo Industries, Inc, distributor of the registered trademark Purell.

Distributed By: GREENBRIER INTERNATIONAL, INC.,

CHESAPEAKE, VA 23320

MADE IN CHINA